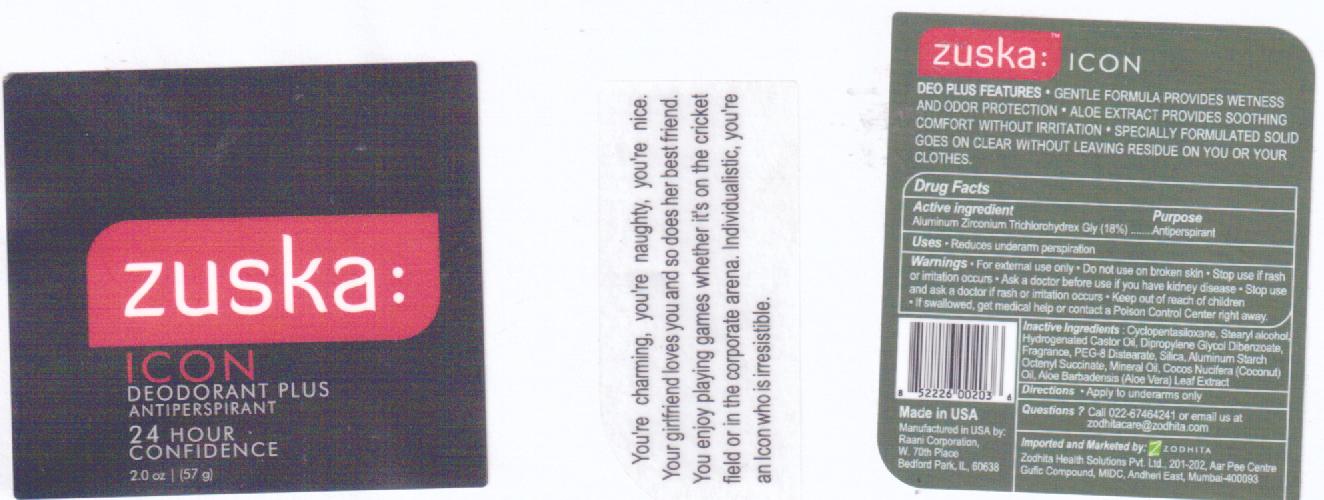 DRUG LABEL: ZUSKA 
NDC: 53135-837 | Form: STICK
Manufacturer: RAANI CORPORATION
Category: otc | Type: HUMAN OTC DRUG LABEL
Date: 20100414

ACTIVE INGREDIENTS: ALUMINUM ZIRCONIUM TRICHLOROHYDREX GLY 180 mg/1 g
INACTIVE INGREDIENTS: CYCLOMETHICONE 5; STEARYL ALCOHOL; HYDROGENATED CASTOR OIL; PEG-8 DISTEARATE; SILICON DIOXIDE; ALUMINUM STARCH OCTENYLSUCCINATE; MINERAL OIL; COCONUT; ALOE VERA LEAF

Drug Facts

Active Ingredients: Aluminum Zirconium Trichlorohydrex Gly (18%)

Purpose: Antiperspirant

WARNINGS

Warnings: For external use only. Do not use on broken skin. Stop us if rash or irritation occurs. Ask a doctor before use if you have kidney disease. Stop use and ask a doctor if rash or irritation occurs. Keep out of reach of children. If swallowed, get medical help or contact a Poison Control Center right away.

DOSAGE AND ADMINISTRATION

Directions: Apply to underarms only

QUESTIONS

Questions?: Call 022-67464241 or email us at zodhitacare@zodhita.com

INACTIVE INGREDIENT

Inactive Ingredients: Cyclopentasiloxane, Stearyl alcohol, Hydrogenated Castor Oil, Dipropylene Glycol Dibenzoate, Fragrance, PEG-8 Distearate, Silica, Aluminum Strach Octenyl Succinate, Mineral Oil, Cocos Nucifera (Coconut) Oil, Aloe Barbadensis (Aloe Vera) Leaf Extract

INDICATIONS AND USAGE

Use: reduces underarm perspiration